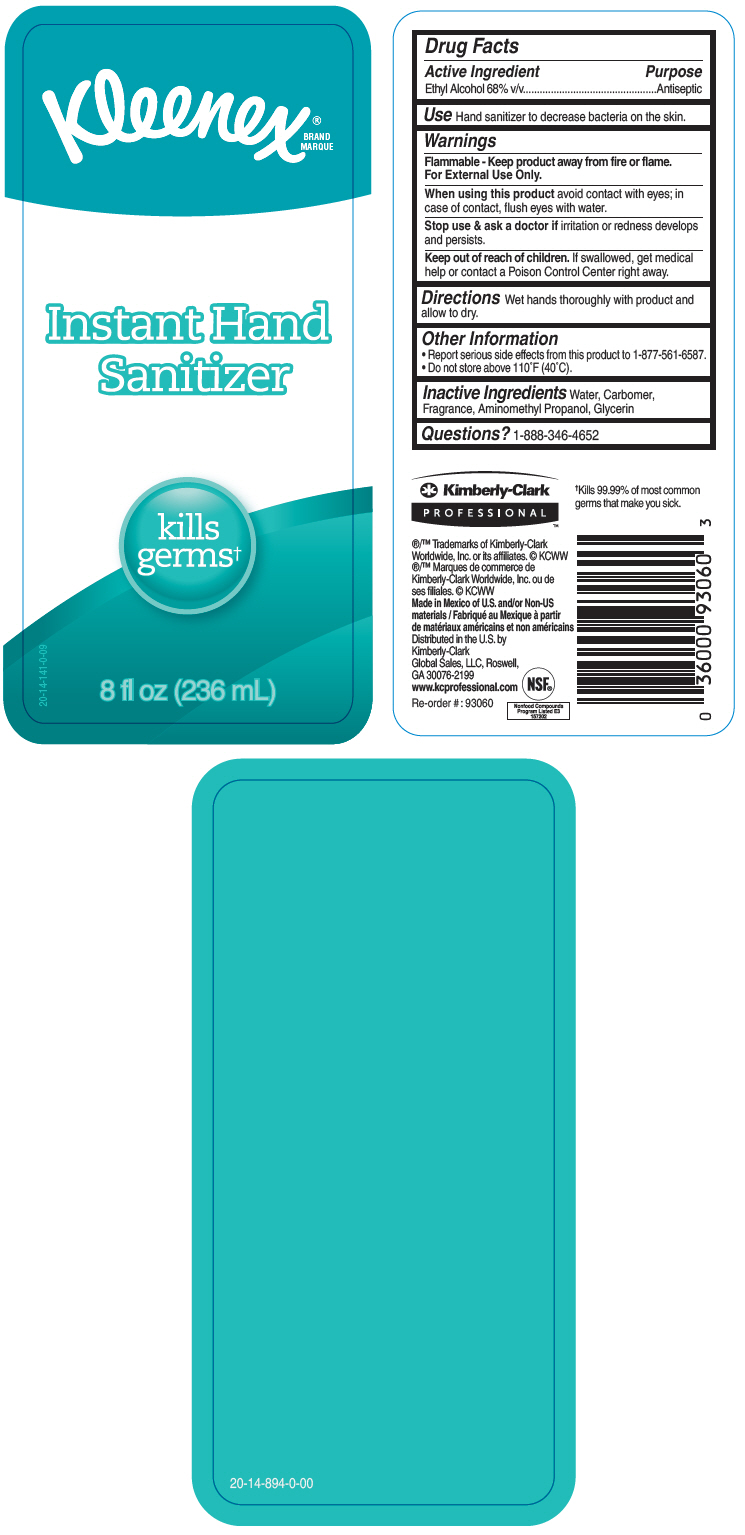 DRUG LABEL: KLEENEX INSTANT HAND SANITIZER
NDC: 55118-704 | Form: SOLUTION
Manufacturer: Kimberly-Clark Corporation
Category: otc | Type: HUMAN OTC DRUG LABEL
Date: 20241210

ACTIVE INGREDIENTS: Alcohol 68 mL/100 mL
INACTIVE INGREDIENTS: WATER; AMINOMETHYLPROPANOL; GLYCERIN; CARBOMER HOMOPOLYMER, UNSPECIFIED TYPE

KLEENEX® INSTANT HAND SANITIZER

Drug Facts

Active Ingredient

Ethyl Alcohol 68% v/v

Purpose

Antiseptic

Use

Hand sanitizer to decrease bacteria on the skin.

Warnings

Flammable - Keep product away from fire or flame.

For External Use Only.

When using this product avoid contact with eyes; in case of contact, flush eyes with water.

Stop use & ask a doctor if irritation or redness develops and persists.

Keep out of reach of children. If swallowed, get medical help or contact a Poison Control Center right away.

Directions

Wet hands thoroughly with product and allow to dry.

Other Information

- Report serious side effects from this product to 1-877-561-6587.
- Do not store above 110°F (40°C).

Inactive Ingredients

Water, Carbomer, Fragrance, Aminomethyl Propanol, Glycerin

Questions?

1-888-346-4652

Distributed in the U.S. by
Kimberly-Clark
Global Sales, LLC, Roswell,
GA 30076-2199

PRINCIPAL DISPLAY PANEL - 236 mL Bottle Label

Kleenex®
BRAND
MARQUE

Instant Hand
Sanitizer

kills
germs†

8 fl oz (236 mL)

20-14-141-0-09